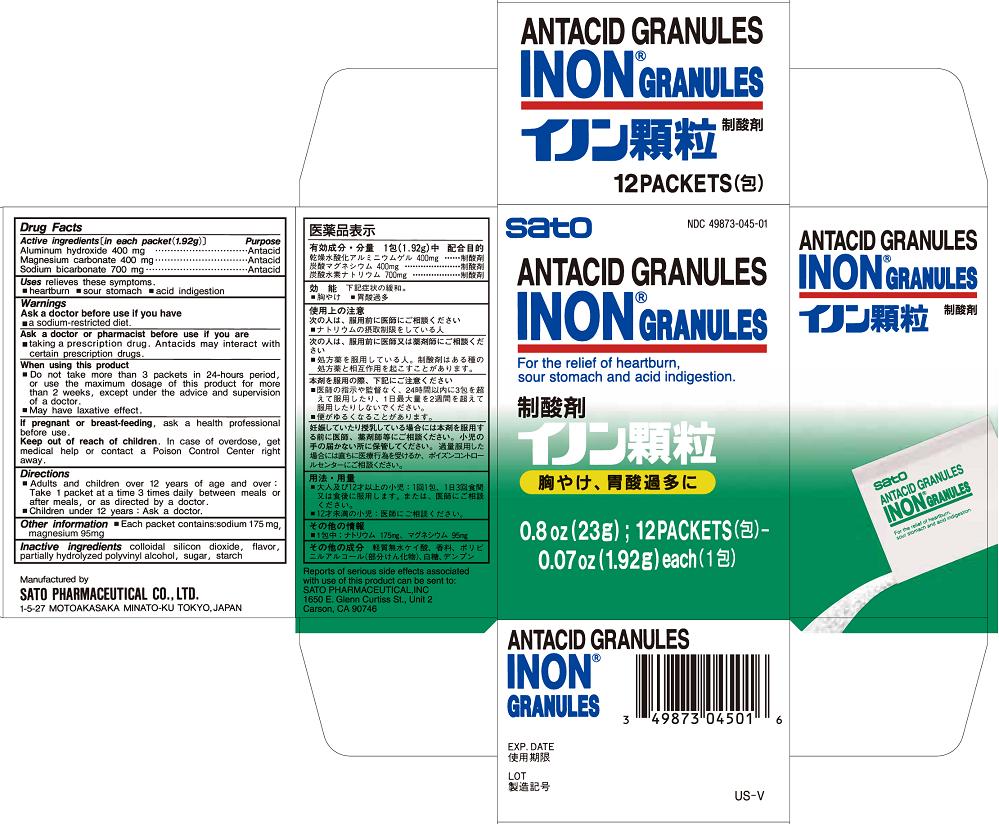 DRUG LABEL: INON
NDC: 49873-045 | Form: GRANULE
Manufacturer: Sato Pharmaceutical Co., Ltd.
Category: otc | Type: HUMAN OTC DRUG LABEL
Date: 20231204

ACTIVE INGREDIENTS: ALUMINUM HYDROXIDE 400 mg/1.92 g; MAGNESIUM CARBONATE 400 mg/1.92 g; SODIUM BICARBONATE 700 mg/1.92 g
INACTIVE INGREDIENTS: SILICON DIOXIDE; POLYVINYL ALCOHOL; SUCROSE; STARCH, POTATO

Inon Granules

Active ingredients [in each packet (1.92g)]
Aluminum hydroxide 400 mg
Magnesium carbonate 400 mg
Sodium bicarbonate 700 mg

Purpose
Aluminum hydroxide Antacid
Magnesium carbonate Antacid
Sodium bicarbonate Antacid

INDICATIONS AND USAGE

Uses relieves these symptoms
■ heartburn ■ sour stomach ■ acid indigestion

Warnings

PREGNANCY OR BREAST FEEDING

If pregnant or breast-feeding, ask a health professional before use.

When using this product
■ Do not take more than 3 packets in 24-hours period, or use the maximum dosage of this product for more than 2 weeks, except under the advice and supervision of a doctor
■ May have laxative effect

Ask a doctor before use if you have
■ a sodium-restricted diet

Ask a doctor or pharmacist before use if you are
■ taking a prescription drug Antacids may interact with certain prescription drugs.

Keep out of reach of children. In case of overdose, get medical help or contact a Poison Control Center right away.

Directions
■ Adults and children 12 years of age and over: Take 1 packet at a time 3 times daily between meals or after meals, or as directed by a doctor
■ Children under 12 years: Ask a doctor

Other information ■ Each packet contains: sodium 175 mg, magnesium 95 mg

INACTIVE INGREDIENT

Inactive ingredients colloidal silicon dioxide, flavor, partially hydrolyzed polyvinyl alcohol, sugar, starch

PACKAGE LABEL

inongrancart.jpg